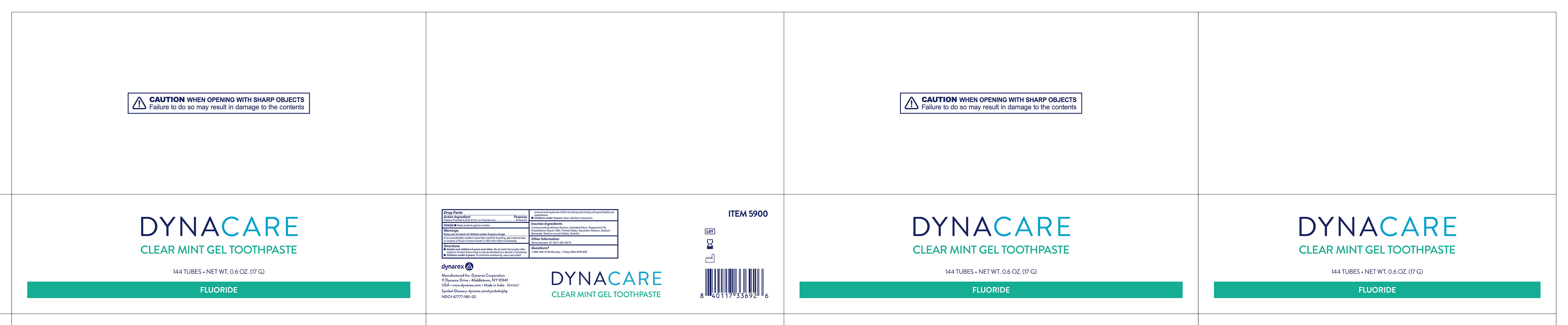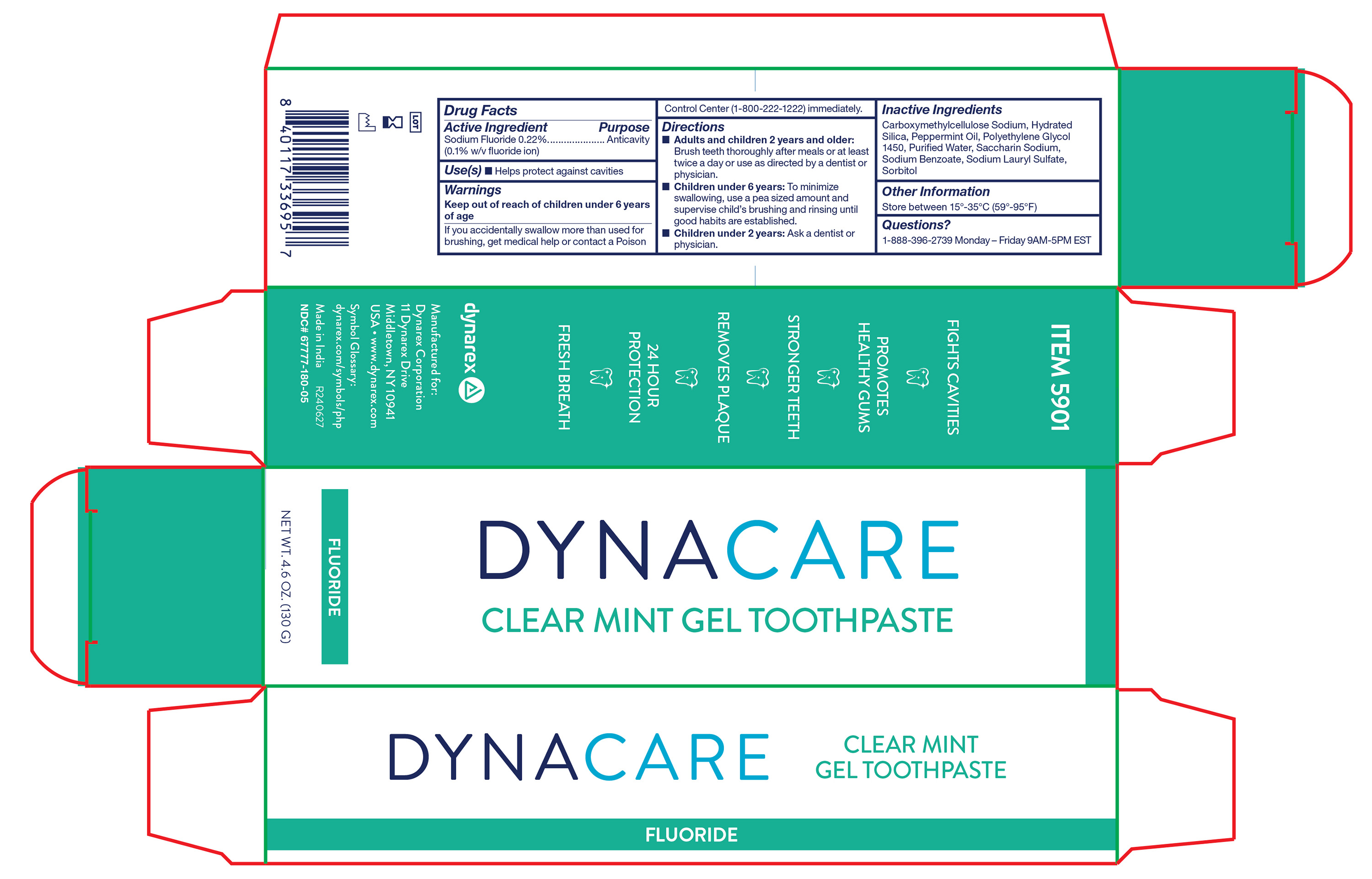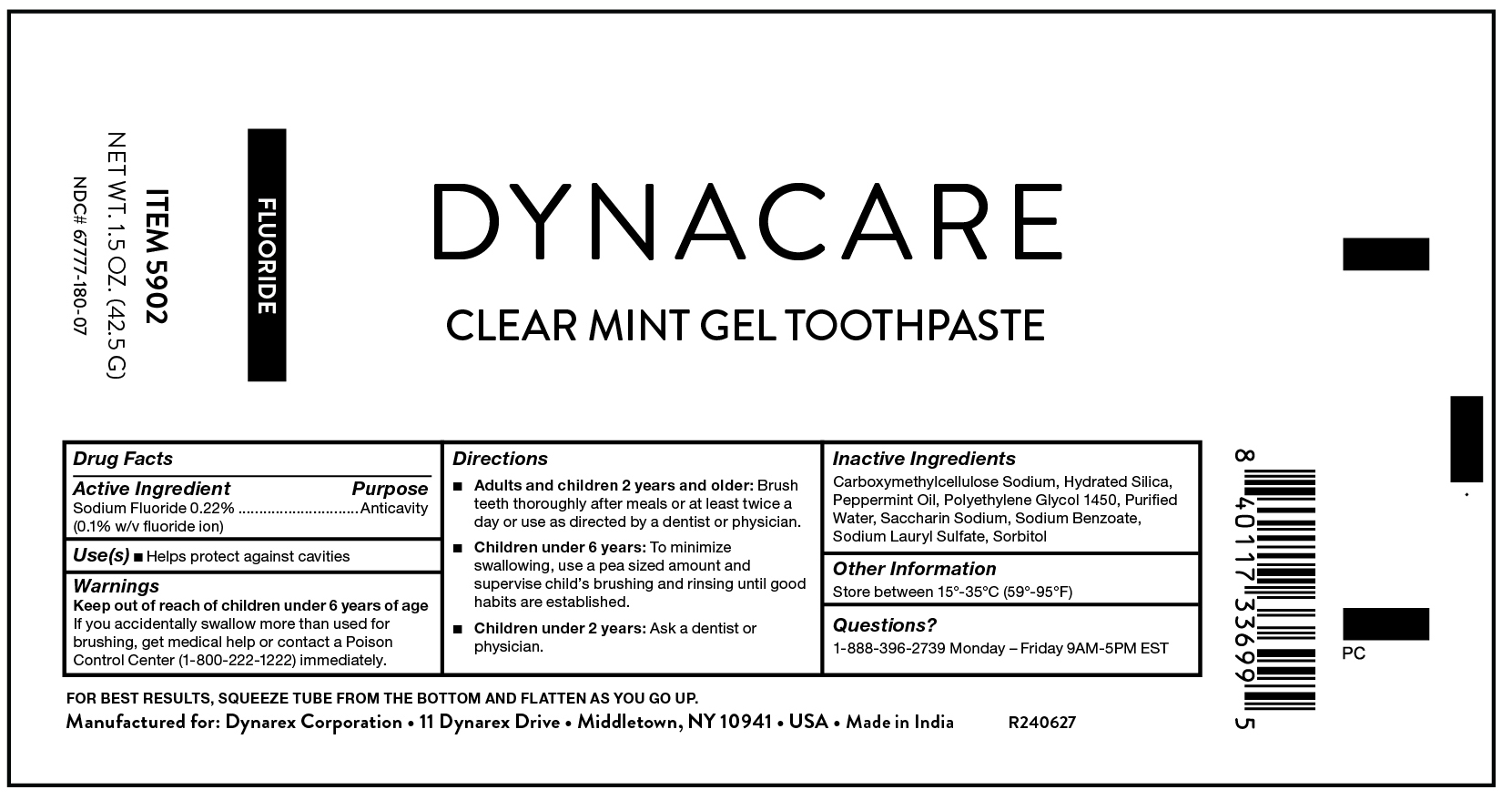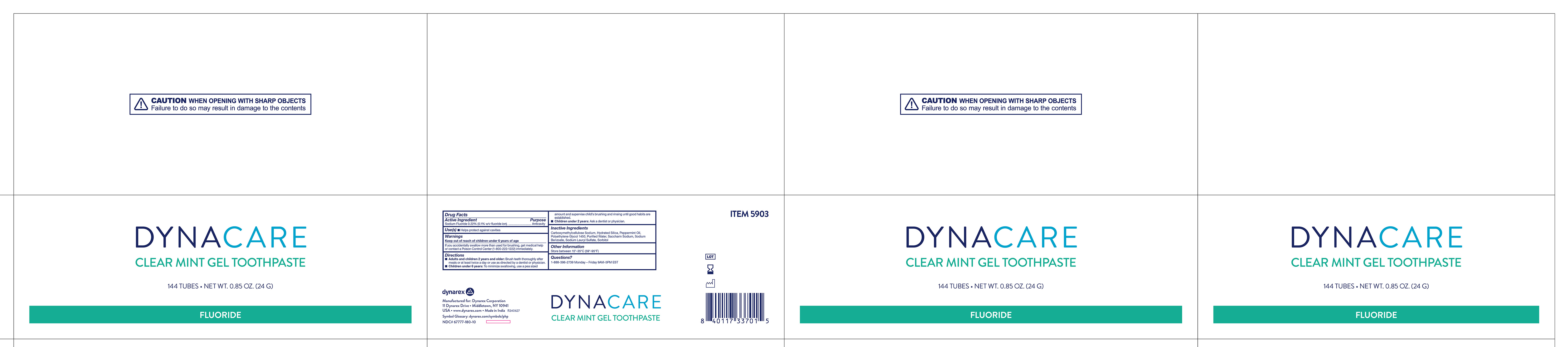 DRUG LABEL: Sodium Fluoride
NDC: 67777-180 | Form: GEL
Manufacturer: Dynarex Corporation
Category: otc | Type: HUMAN OTC DRUG LABEL
Date: 20240627

ACTIVE INGREDIENTS: SODIUM FLUORIDE 220 mg/1 g
INACTIVE INGREDIENTS: PEPPERMINT OIL; SODIUM BENZOATE; POLYETHYLENE GLYCOL 1450; HYDRATED SILICA; CARBOXYMETHYLCELLULOSE SODIUM, UNSPECIFIED; WATER; SODIUM LAURYL SULFATE; SACCHARIN SODIUM; SORBITOL

5900 Clear Mint, Gel Toothpaste, 0.6oz.
5901 Clear Mint, Gel Toothpaste, 4.6oz.
5902 Glear Mint, Gel Toothpaste, 1.5oz.
5903 Clear Mint, Gel Toothpaste, 0.85oz

Active Ingredient

Sodium Fluoride 0.22% (0.1% w/v fluoride ion)

Purpose

Anticavity

Use(s)

Helps protect against cavities

Warnings

If you accidentally swallow more than used for brushing, get medical help or contact a Poison Control Center (1-800-222-1222) immediately.

Keep out of reach of children under 6 years of age

Directions

• Adults and children 2 years of age and older: Brush teeth thoroughtly after meals or at least twice a day or use as directed by a dentist or physician.

• Children under 6 years: To minimize swallowing, use a pea sized amount and supervise child's brushing and rinsing until good habits are established.

• Children under 2 years: Ask a dentist or physician.

Inactive Ingredients

Carboxymethylcellulose Sodium, Hydrated Silica, Peppermint Oil, Polyethylene Glycol 1450, Purified Water, Saccharin Sodium, Sodium Benzoate, Sodium Lauryl Sulfate, Sorbitol

Other Information

Store between 15º-35ºC (59º-95ºF)

Questions?

1-888-396-2739 Monday - Friday 9AM - 5PM EST

Label 5900

5900 Clear Mint, Gel Toothpaste

Label 5901

5901 Clear Mint, Gel Toothpaste

Label 5902

5902 Clear Mint, Gel Toothpaste

Label 5903

5903 Clear Mint, Gel Toothpaste